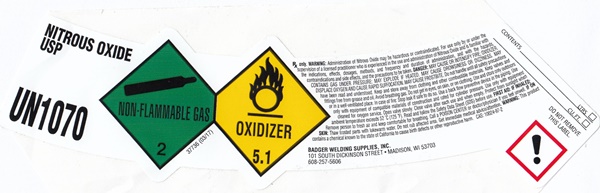 DRUG LABEL: NITROUS OXIDE

NDC: 12121-002 | Form: GAS
Manufacturer: Badger Welding Supplies, Inc.
Category: prescription | Type: HUMAN PRESCRIPTION DRUG LABEL
Date: 20260212

ACTIVE INGREDIENTS: NITROUS OXIDE 99 L/100 L

NITROUS OXIDE USP - 002

NITROUS OXIDE USP LABEL

NITROUS OXIDE USP

UN1070

NON-FLAMMABLE GAS 2

OXIDIZER 5.1

37736 (0317)

Rx only. WARNING:Administration of Nitrous Oxide may be hazardous or contraindicated. For use only by or under the supervision of a licensed practitioner who is experienced in the use and administration of Nitrous Oxide and is familiar with the indications, effects, dosages, methods, and frequency and duration of administration, and with the hazards, contraindications and side effects, and the precautions to be taken. DANGER:MAY CAUSE OR INTENSIFY FIRE; OXIDIZER CONTAINS GAS UNDER PRESSURE; MAY EXPLODE IF HEATED. MAY CAUSE DROWSINESS OR DIZZINESS. MAY DISPLACE OXYGEN AND CAUSE RAPID SUFFOCATION. MAY CAUSE FROSTBITE. Do not handle until all safety precautions have been read and understood. Keep and store away from clothing and other combustible materials. Keep valves and fittings free from grease and oil. Avoid breathing gas. Do not get in eyes, on skin or on clothing. Use an store only outdoors or in a well ventillated place. In case of fire: Stop leak if safe to do so. Use a back flow preventive device in the piping. Use only equipment of compatible materials of construction and rated for cylinder pressure. Use only with equipment cleaned for oxygen service. Open valve slowly. Close valve after each use and when empty. Protect from sunlight when ambient temperature exceeds 52°C (125°F). Read and follow the Safety Data Sheet (SDS) before use. FIRST AID: IF INHALED:Remove person to fresh air and keep comfortable for breathing. Call a POISON CENTER or doctor/physician if you feel unwell. IF ON SKIN:Thaw frozen parts with lukewarm water. Do not rub affected area. Get immediate medical advice.attention. WARNING:This product contains a chemical known to the state of Califorina to cause birth defects or other reproductive harm. CAS: 10024-97-2

BADGER WELDING SUPPLIES, INC.

101 SOUTH DICKINSON STREET • MADISON WI 53704

608-257-5606

DO NOT REMOVE THIS LABEL

CONTENTS ________________________ LTRS. ____________________________________CU. FT.